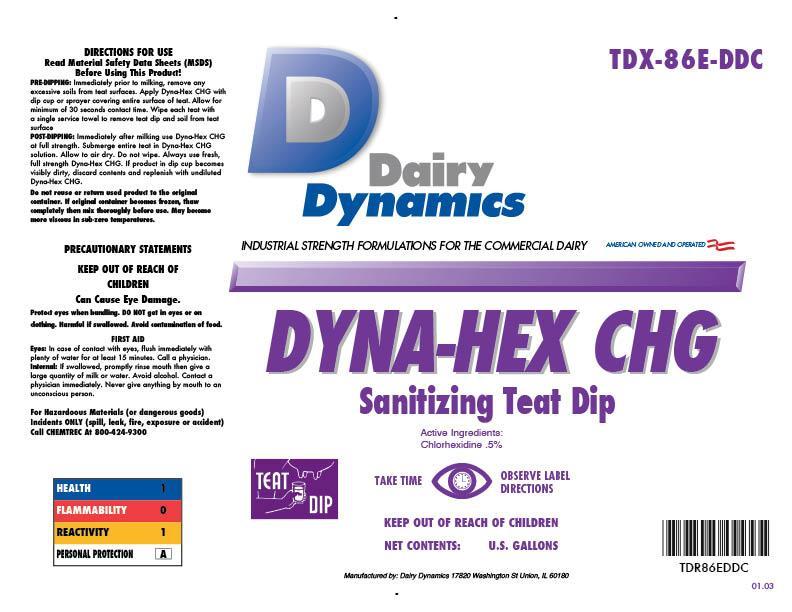 DRUG LABEL: DYNA-HEX CHG
NDC: 67351-986 | Form: SOLUTION
Manufacturer: Dairy Dynamics L.L.C.
Category: animal | Type: OTC ANIMAL DRUG LABEL
Date: 20150115

ACTIVE INGREDIENTS: CHLORHEXIDINE GLUCONATE 2.9 g/1 L
INACTIVE INGREDIENTS: WATER; SODIUM HYDROXIDE; HYDROXYETHYL CELLULOSE (1500 MPA.S AT 1%); PROPYLENE GLYCOL; DIDECYLDIMONIUM CHLORIDE; C9-11 PARETH-3; LANOLIN; AMMONIUM CHLORIDE; FD&C BLUE NO. 1

Dairy Dynamics
DYNA-HEX CHG
Sanitizing Teat Dip

DIRECTIONS FOR USE

Read Material Safety Data Sheets (MSDS) Before Using This Product!

PRE-DIPPING: Immediately prior to milking, remove any excessive soils from teat surfaces. Apply Dyna-Hex CHG with dip cup or sprayer covering entire surface of teat. Allow for minimum of 30 seconds contact time. Wipe each teat with a single service towel to remove teat dip and soil from teat surface.

POST-DIPPING: Immediately after milking use Dyna-Hex CHG at full strength. Submerge entire teat in Dyna-Hex CHG solution. Allow to air dry. Do not wipe. Always use fresh, full strength Dyna-Hex CHG. If product in dip cup becomes visibly dirty, discard contents and replenish with undiluted Dyna-Hex CHG.

Do not reuse or return used product to the original container. If original container becomes frozen, thaw completely then mix thoroughly before use. May become more viscous at sub-zero temperatures.

PRECAUTIONS

PRECAUTIONARY STATEMENTS

KEEP OUT OF REACH OF CHILDREN

Can Cause Eye Damage.

Protect eyes when handling. DO NOT get in eyes or on clothing. Harmful if swallowed. Avoid contamination of food.

FIRST AID

Eyes: in case of contact with eyes, flush immediately with plenty of water for at least 15 minutes. Call a physician.

Internal: if swallowed, promptly rinse mouth then give a large quantity of water. Avoid alcohol. Contact a physician immediately. Never give anything by mouth to an unconscious person.

For Hazardous Materials (or dangerous goods) Incidents ONLY (spill, leak, fire, exposure or accident) Call CHEMTREC At 800-424-9300

HEALTH 1

FLAMMABILITY 1

REACTIVITY 1

PERSONAL PROTECTION 1

Dairy Dynamics

INDUSTRIAL STRENGTH FORMULATIONS FOR THE COMMERCIAL DAIRY

AMERICAN OWNED AND OPERATED

Active Ingredients: Chlorhexidine .5%

TEAT DIP

TAKE TIME OBSERVE LABEL DIRECTIONS

KEEP OUT OF REACH OF CHILDREN

NET CONTENTS: U.S. GALLONS

Manufactured by: Dairy Dynamics 17820 Washington St Union, IL 60180

TDX-86E-DDC

TDX86EDDC